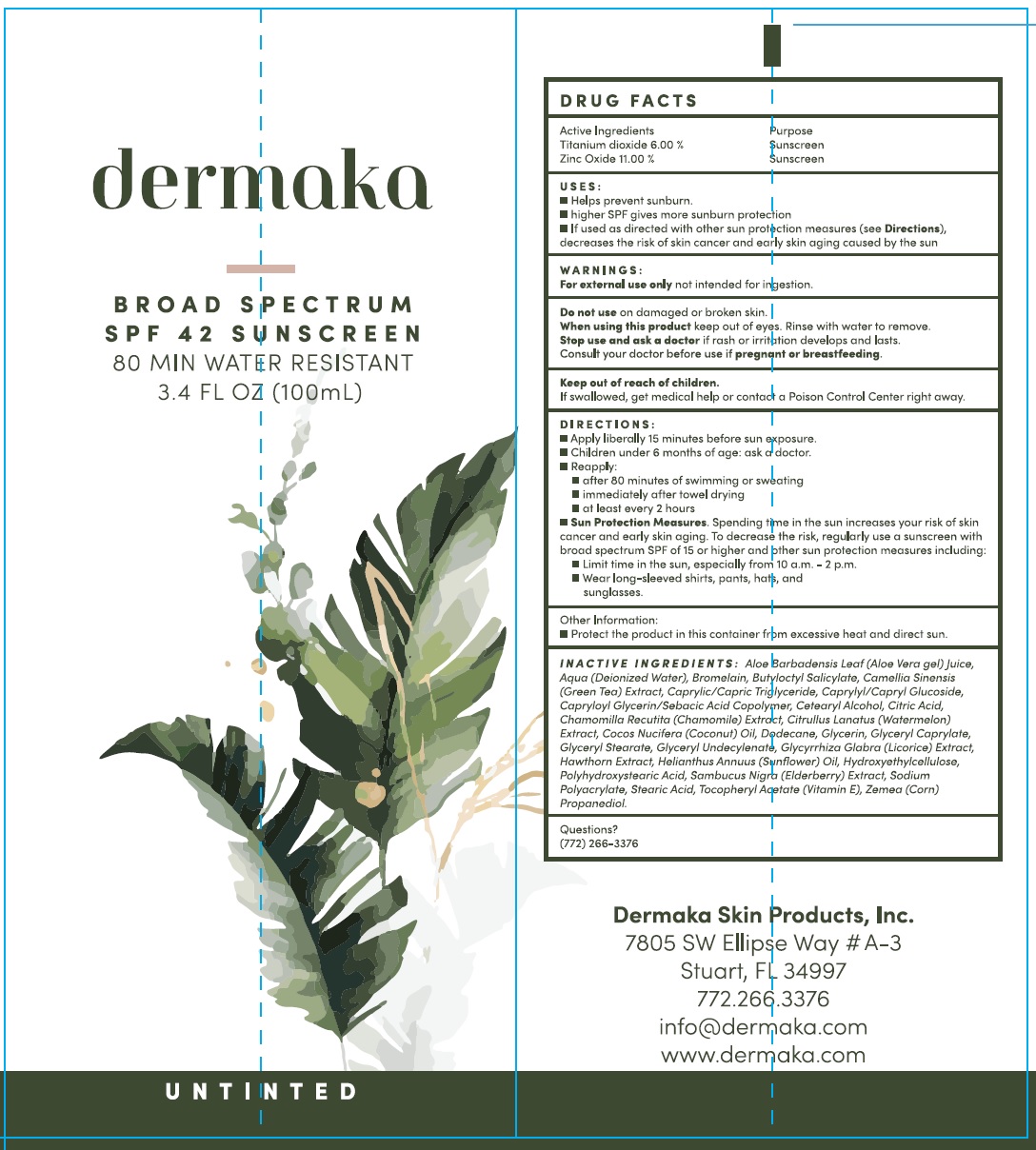 DRUG LABEL: DERMAKA Broad Spectrum SPF-42 Sunscreen Untinted
NDC: 82240-424 | Form: CREAM
Manufacturer: DERMAKA SKIN PRODUCTS
Category: otc | Type: HUMAN OTC DRUG LABEL
Date: 20231111

ACTIVE INGREDIENTS: TITANIUM DIOXIDE 60 mg/1 mL; ZINC OXIDE 110 mg/1 mL
INACTIVE INGREDIENTS: ALOE VERA LEAF; WATER; BROMELAINS; BUTYLOCTYL SALICYLATE; GREEN TEA LEAF; MEDIUM-CHAIN TRIGLYCERIDES; CAPRYLYL/CAPRYL OLIGOGLUCOSIDE; CETOSTEARYL ALCOHOL; CITRIC ACID MONOHYDRATE; CHAMOMILE; WATERMELON; COCONUT; DODECANE; GLYCERIN; GLYCERYL CAPRYLATE; LICORICE; HELIANTHUS ANNUUS FLOWERING TOP; HYDROXYETHYL CELLULOSE, UNSPECIFIED; STEARIC ACID; .ALPHA.-TOCOPHEROL ACETATE; CORN

DERMAKA Broad Spectrum SPF-42 Sunscreen Untinted

Active Ingredients

Titanium dioxide 6.00%

Zinc Oxide 11.00%

Purpose

Sunscreen

USES:

- Helps prevent sunburn.
- higher SPF gives more sunburn protection
- If used as directed with other sun protection measures (see), decreases the risk of skin cancer and early skin aging caused by the sun Directions

WARNINGS:

not intended for ingestion. For external use only

Do not use

on damaged or broken skin.

When using this product

keep out of eyes. Rinse with water to remove.

Stop use and ask a doctor if

rash or irritation develops and lasts.

Consult your doctor before use if

Keep out of reach of children.

If swallowed, get medical help or contact a Poison Control Center right away.

DIRECTIONS:

- Apply liberally 15 minutes before sun exposure.
- Children under 6 months of age: ask a doctor.
- Reapply:
- after 80 minutes of swimming or sweating
- immediately after towel drying
- at least every 2 hours
- Spending time in the sun increases your risk of skin cancer and early skin aging. To decrease this risk, regularly use sunscreen with a broad spectrum SPF of 15 or higher and other sun protection measures including: Sun Protection Measures.
- Limit time in the sun, especially from 10 a.m. – 2 p.m.
- Wear long-sleeved shirts, pants, hats, and sunglasses.

Other Information:

- Protect the product in this container from excessive heat and direct sun.

INACTIVE INGREDIENTS

Aloe Barbadensis Leaf (Aloe Vera gel) Juice, Aqua (Deionized Water), Bromelain, Butyloctyl Salicylate, Camellia Sinensis (Green Tea) Extract, Caprylic/Capric Triglyceride, Caprylyl/Capryl Glucoside, Capryloyl Glycerin/Sebacic Acid Copolymer, Cetearyl Alcohol, Citric Acid, Chamomilla Recutita (Chamomile) Extract, Citrullus Lanatus (Watermelon) Extract, Cocos Nucifera (Coconut) Oil, Dodecane, Glycerin, Glyceryl Caprylate, Gleceryl Stearate, Glyceryl Undecylenate, Glyyrrhiza Glabra (Licorice) Extract, Hawthorn Exract, Helianthus Annuus (Sunflower) Oil, Hydroxyethylcellulose, Polyhydroxystearic Acid, Sambucus Nigra (Elderberry)Extract, Sodium Polyacrylate, Stearic Acid, Tocopheryl Acetate (Vitamin E), Zemea (Corn) Propanediol.

Questions?

(772) 266-3376